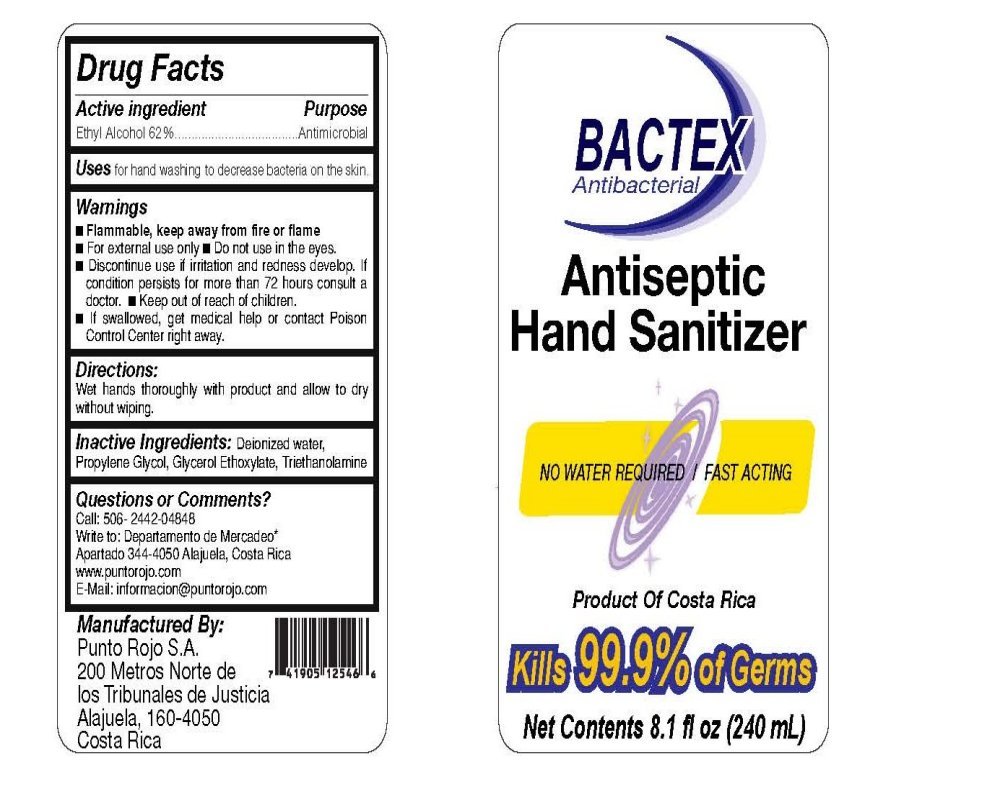 DRUG LABEL: BACTEX  Antiseptic Hand Sanitizer
NDC: 49839-100 | Form: GEL
Manufacturer: Punto Rojo, S.A
Category: otc | Type: HUMAN OTC DRUG LABEL
Date: 20091002

ACTIVE INGREDIENTS: ALCOHOL 62 mL/100 mL
INACTIVE INGREDIENTS: WATER; PROPYLENE GLYCOL; TROLAMINE

BACTEX Antibacterial Antiseptic Hand Sanitizer

Drug Facts

Active Ingredient Purpose

Ethyl Alcohol 62 percent Antimicrobial

PURPOSE

Uses for hand washing to decrease bacteria on the skin.

Warnings

Flammable, keep away from fire or flame

For external use only

Do not use in the eyes

Discontinue use if irritation and redness develop. If condition persists for more than 72 hours consult a doctor.

Keep out of the reach of children.

If swallowed, get medical help or contact Poison Control Center right away.

Directions:

Wet hands thoroughly with product and allow to dry without wiping.

Inactive Ingredients:

Deionized water, Propylene Glycol, Glycerol Ethoxylate, Triethanolamine

Questions or Comments

Call: 506 2442 04848

Write to: Departamento de Mercadeo

Apartado 344-4050 Alajuela, Costa Rica

www.puntorojo.com

Email: informacion@puntorojo.com

DESCRIPTION

Manufactured By:

Punto Rojo S.A.

200 Metros Norte de

los Tribunales de Justicia

Alajuela, 160-4050

Costa Rica

PACKAGE LABEL

BACTEX
Antibacterial
Antiseptic
Hand Sanitizer
NO WATER REQUIRED
FAST ACTING
Product Of Costa Rica
Kills 99.9 percent of Germs
Net Contents 8.1 fl oz 240 mL